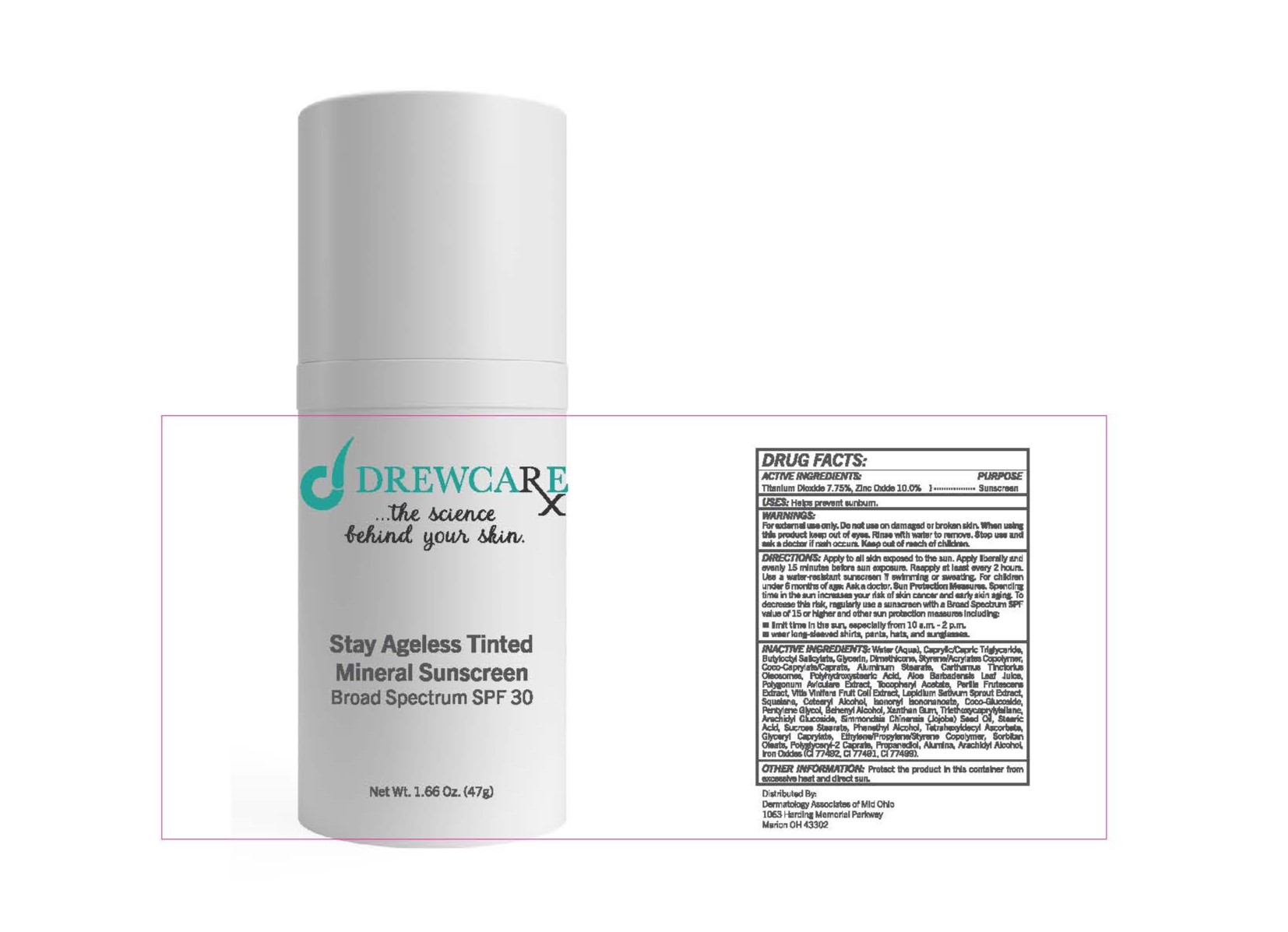 DRUG LABEL: Stay Ageless Tinted Mineral Sunscreen Broad Spectrum SPF30
NDC: 83181-0651 | Form: CREAM
Manufacturer: DERM ASSO. MID OHIO
Category: otc | Type: HUMAN OTC DRUG LABEL
Date: 20250131

ACTIVE INGREDIENTS: TITANIUM DIOXIDE 7.75 g/100 g; ZINC OXIDE 10 g/100 g
INACTIVE INGREDIENTS: WATER; MEDIUM-CHAIN TRIGLYCERIDES; BUTYLOCTYL SALICYLATE; GLYCERIN; DIMETHICONE; COCOYL CAPRYLOCAPRATE; ALUMINUM STEARATE; CARTHAMUS TINCTORIUS SEED OLEOSOMES; ALOE VERA LEAF; POLYGONUM AVICULARE TOP; .ALPHA.-TOCOPHEROL ACETATE; GARDEN CRESS SPROUT; SQUALANE; CETOSTEARYL ALCOHOL; ISONONYL ISONONANOATE; COCO GLUCOSIDE; PENTYLENE GLYCOL; DOCOSANOL; XANTHAN GUM; TRIETHOXYCAPRYLYLSILANE; ARACHIDYL GLUCOSIDE; JOJOBA OIL; STEARIC ACID; SUCROSE STEARATE; PHENYLETHYL ALCOHOL; TETRAHEXYLDECYL ASCORBATE; GLYCERYL MONOCAPRYLATE; SORBITAN MONOOLEATE; POLYGLYCERYL-2 CAPRATE; PROPANEDIOL; ALUMINUM OXIDE; ARACHIDYL ALCOHOL; FERRIC OXIDE YELLOW; FERRIC OXIDE RED; FERROSOFERRIC OXIDE

Tinted Mineral Defense Broad Spectrum SPF 30 Sunscreen

DRUG FACTS:

ACTIVE INGREDIENTS

Titanium Dioxide 7.75%, Zinc Oxide 10.0%.

Purpose

Sunscreen

USES

Helps prevent sunburn.

WARNINGS

For external use only. Do not use on damaged or broken skin. When using this product keep out of eyes. Rinse with water to remove. Stop use and ask a doctor if rash occurs.

Keep out of reach of children.

DIRECTIONS

Apply to all skin exposed to the sun. *Apply liberally and evenly 15 minutes before sun exposure. *Reapply at least every 2 hours. *Use a water-resistant sunscreen if swimming or sweating. *For children under 6 months of age: Ask a doctor. Sun Protection Measures. Spending time in the sun increases your risk of skin cancer and early skin aging. To decrease this risk, regularly use a sunscreen with a Broad Spectrum SPF value of 15 or higher and other sun protection measures including:

- limit time in the sun, especially from 10 a.m. - 2 p.m.
- wear long-sleeved shirts, pants, hats, and sunglasses.

INACTIVE INGREDIENTS

Water (Aqua), Caprylic/Capric Triglyceride, Butyloctyl Salicylate, Glycerin, Dimethicone, Styrene/Acrylates Copolymer, Coco-Caprylate/Caprate, Aluminum Stearate, Carthamus Tinctorius Oleosomes, Polyhydroxystearic Acid, Aloe Barbadensis Leaf Juice, Polygonum Aviculare Extract, Tocopheryl Acetate, Perilla Frutescens Extract, Vitis Vinifera Fruit Cell Extract, Lepidium Sativum Sprout Extract, Squalane, Cetearyl Alcohol, Isononyl Isononanoate, Coco-Glucoside, Pentylene Glycol, Behenyl Alcohol, Xanthan Gum, Triethoxycaprylylsilane, Arachidyl Glucoside, Simmondsia Chinensis (Jojoba) Seed Oil, Stearic Acid, Sucrose Stearate, Phenethyl Alcohol, Tetrahexyldecyl Ascorbate, Glyceryl Caprylate, Ethylene/Propylene/Styrene Copolymer, Sorbitan Oleate, Polyglyceryl-2 Caprate, Propanediol, Alumina, Arachidyl Alcohol, Iron Oxides (CI 77492, CI 77491, CI 77499).

OTHER INFORMATION

Protect the product in this container from excessive heat and direct sun.

See Beyond

Stay Ageless

Tinted Mineral

Broad Spectrum

Sunscreen SPF 30